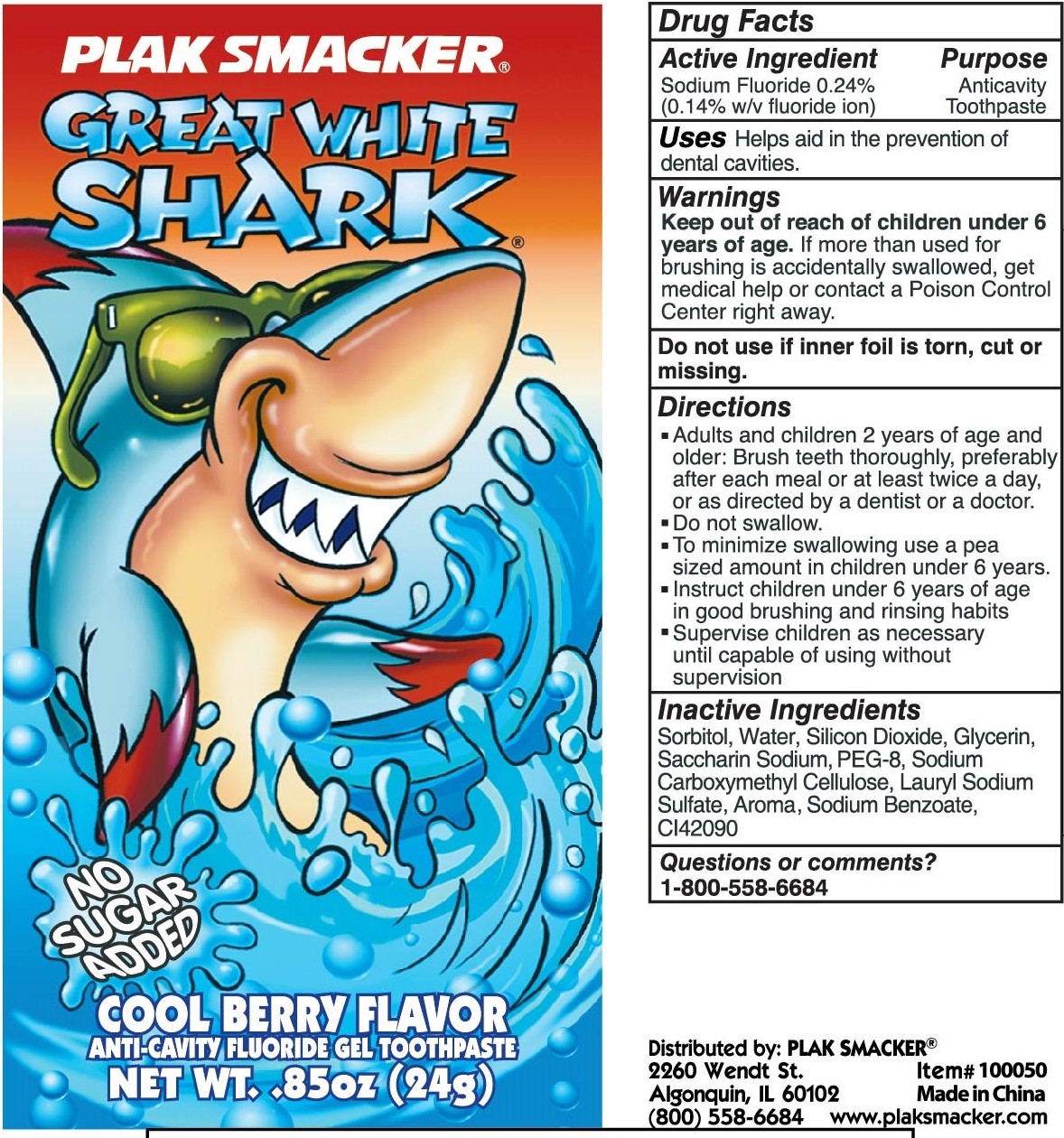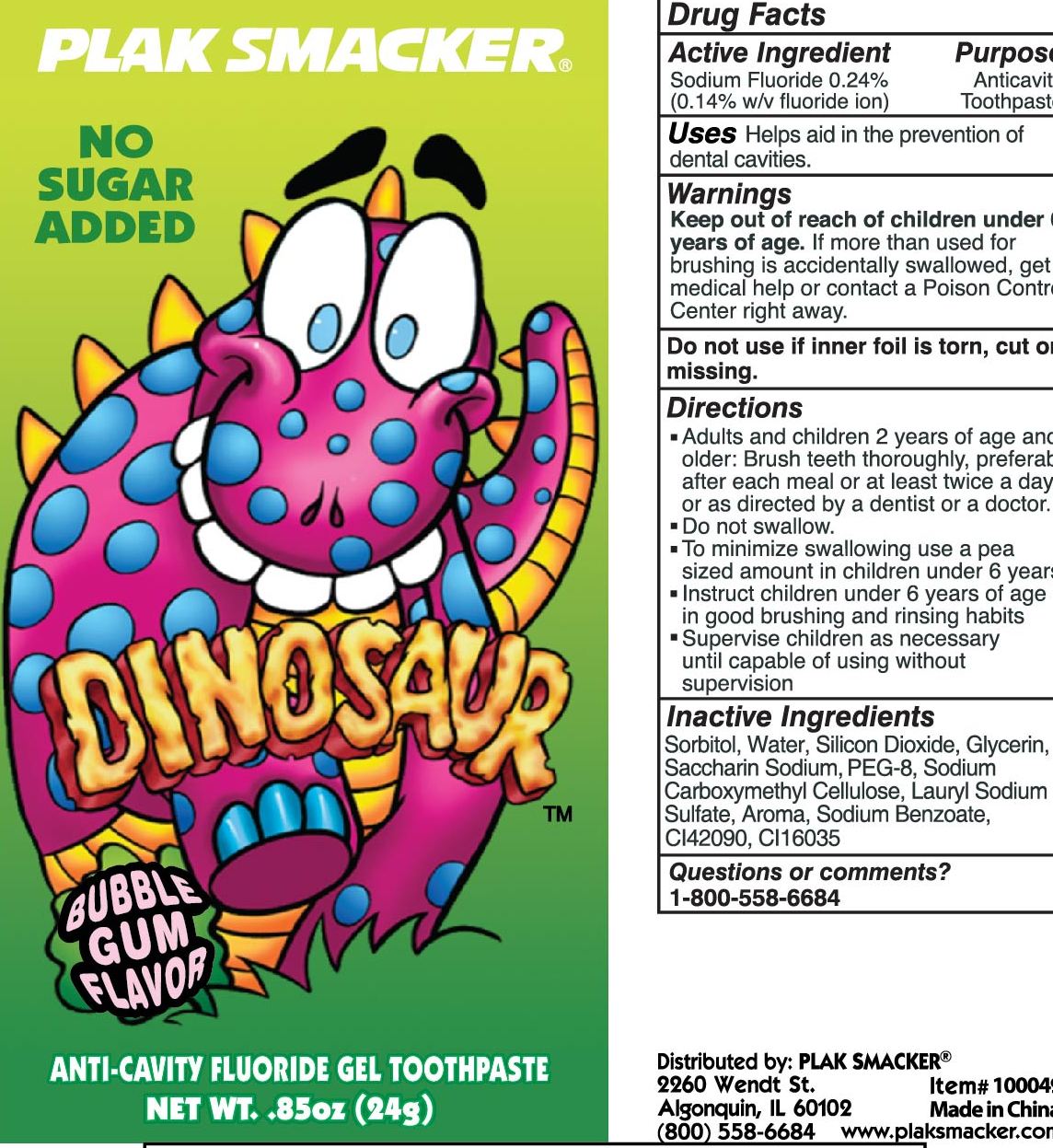 DRUG LABEL: PLAK SMACKER Anti-cavity Fluoride Gel
NDC: 71167-005 | Form: PASTE
Manufacturer: HUAIAN ZONGHENG BIO-TECH CO., LTD
Category: otc | Type: HUMAN OTC DRUG LABEL
Date: 20180314

ACTIVE INGREDIENTS: SODIUM FLUORIDE 0.24 g/100 g
INACTIVE INGREDIENTS: SODIUM BENZOATE; SORBITOL, L-; WATER; SILICON DIOXIDE; GLYCERIN; PEG-8 DIOLEATE; DISODIUM CARBOXYMETHYLARSONATE; SODIUM LAURYL SULFATE; AROMADENDRIN; SACCHARIN SODIUM

71167-005 PLAK SMACKER 0.24

Active Ingredient

sodium fluoride 0.24%（0.14% w/v fluoride ion）

Purpose

Anticavitytoothpaste

Use

helps aid in the prevention of dental cavities.

Warning

Keep out of reach of children under 6 years of age.
If more than used for brushing is accidently swallowed get medical help or contact a poison control center right away.

Directions

Adults and children 6 years of age and older:brush teeth thoroughly, after meals or at least twice a day or use as directed by a dentist.

do not swallow

to minimize swallowing use a pea-sized amount in children under 6

supervise children as necessary until capable of using without supervision

Inactive Ingredients

sorbitl,water,silicon dioxide,glycerin,saccharin sodium,PEG-8,sodium carboxymethyl cellulose ,lauryl sodium sulfate,aroma,sodium benzoate,ci42090anium Dioxide),Sodium saccharin,rose canina fruit oil

Keep out of reach of children under 6 years of age